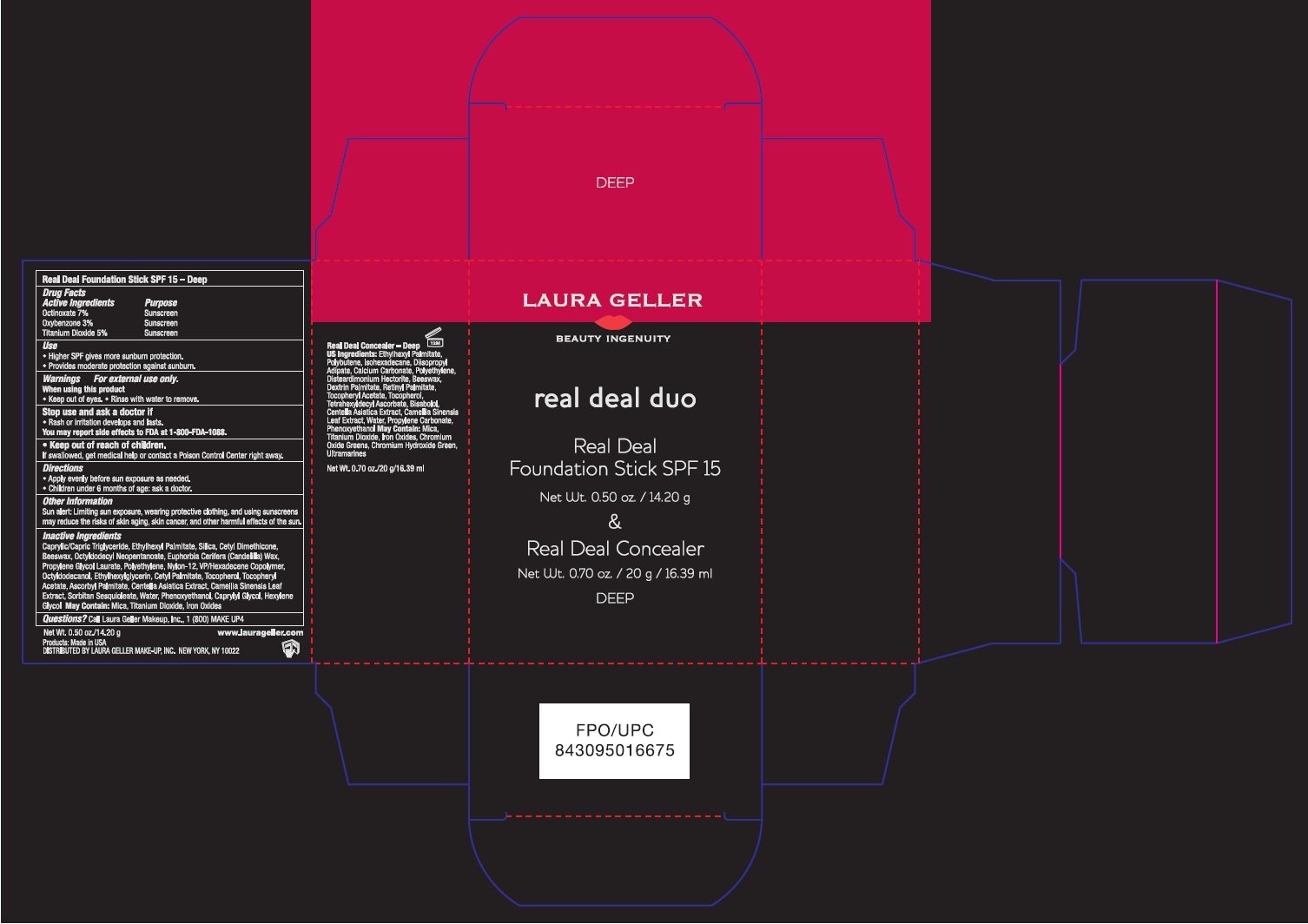 DRUG LABEL: Real Deal Foundation
NDC: 51389-107 | Form: STICK
Manufacturer: LAURA GELLER MAKE UP INC.
Category: otc | Type: HUMAN OTC DRUG LABEL
Date: 20111113

ACTIVE INGREDIENTS: OCTINOXATE 7 g/100 g; OXYBENZONE 3 g/100 g; TITANIUM DIOXIDE 5 g/100 g
INACTIVE INGREDIENTS: MEDIUM-CHAIN TRIGLYCERIDES; ETHYLHEXYL PALMITATE; SILICON DIOXIDE; YELLOW WAX; OCTYLDODECYL NEOPENTANOATE; CANDELILLA WAX; PROPYLENE GLYCOL LAURATES; HIGH DENSITY POLYETHYLENE; OCTYLDODECANOL; ETHYLHEXYLGLYCERIN; CETYL PALMITATE; TOCOPHEROL; ALPHA-TOCOPHEROL ACETATE; ASCORBYL PALMITATE; CENTELLA ASIATICA; GREEN TEA LEAF; SORBITAN SESQUIOLEATE; WATER; PHENOXYETHANOL; CAPRYLYL GLYCOL; HEXYLENE GLYCOL

Drug Facts

Active Ingredients

Octinoxate 7%
Oxybenzone 3%
Titanium Dioxide 5%

Purpose

Sunscreen

Use

- Higher SPF gives more sunburn protection.

- Provides moderate protection against sunburn.

Warnings

For external use only.

When using this product

- Keep out of eyes.
- Rinse with water to remove.

Stop use and ask a doctor if

- Rash or irritation develops and lasts.

You may report side effect to FDA at 1-800-FDA-1088.

- Keep out of reach of children.

If swallowed, get medical help or contact a Poison Control Center right away.

Directions

- Apply evenly before sun exposure as needed.
- Children under 6 months of age: ask a doctor.

Other Information

Sun alert: Limiting sun exposure, wearing protective clothing, and using sunscreens may reduce the risks of skin aging, skin cancer, and other harmful effects of the sun.

Inactive Ingredients

Caprylic/Capric Triglyceride, Ethylhexyl Palmitate, Silica, Cetyl Dimethicone, Beeswax, Octyldodecyl Neopentanoate, Euphorbia Cerifera (Candelilla) Wax, Propylene Glycol Laurate, Polyethylene, Nylon-12, VP/Hexadecene Copolymer,Octyldodecanol, Ethylhexylglycerin, Cetyl Palmitate, Tocopherol, Tocopheryl Acetate, Ascorbyl Palmitate, Cantella Asiatica Extract, Camellia Sinensis Leaf Extract, Sorbitan Sesquioleate, Water, Phenoxyethanol, Caprylyl Glycol, Hexylene Glycol. May Contain: Mica, Titanium Dioxide, Iron Oxides.

Questions?

Call Laura Geller Make-up, Inc., 1(800) MAKE UP4

Principal Display Panel

LAURA GELLER
BEAUTY INGENUITY
real deal duo
Real Deal
Foundation Stick SPF 15
Net. Wt. 0.50 oz. / 14.20 g
&
Real Deal Concealer
Net. Wt. 0.70 oz. / 20 g / 16.39 ml
DEEP